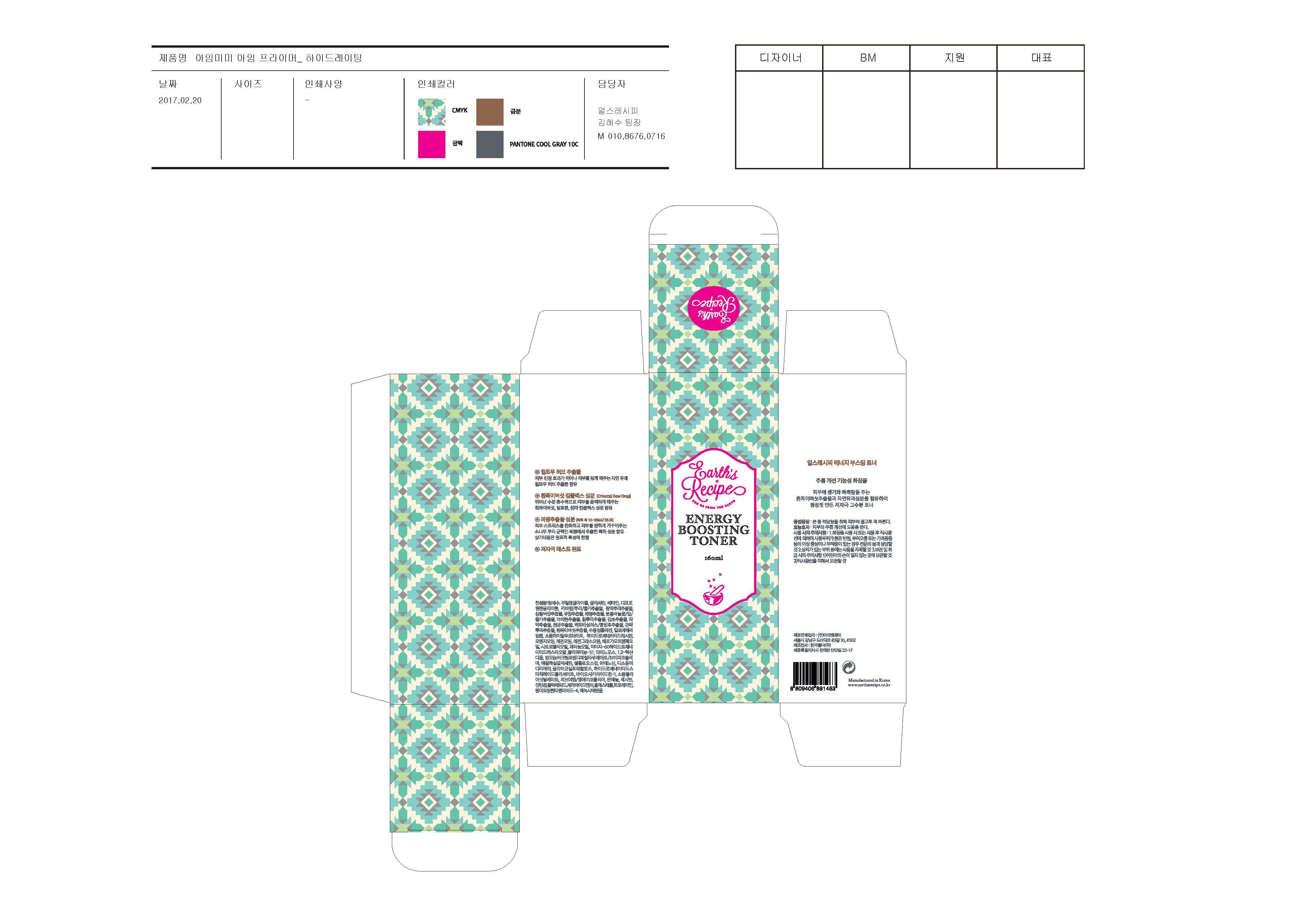 DRUG LABEL: Energy Boosting Toner
NDC: 71496-0002 | Form: LIQUID
Manufacturer: ARI&J Inc
Category: otc | Type: HUMAN OTC DRUG LABEL
Date: 20170704

ACTIVE INGREDIENTS: ADENOSINE 0.04 g/100 mL; TREMELLA FUCIFORMIS WHOLE 0.1 g/100 mL; CERAMIDE NP 0.01 g/100 mL
INACTIVE INGREDIENTS: BUTYLENE GLYCOL; GLYCERIN; WATER

ACTIVE INGREDIENT

Tremella Fuciformis Whole, Adenosine, Ceramide

INACTIVE INGREDIENT

Water, Glycerin, Butylene Glycol, etc

PURPOSE

Skin protectant - Anti Wrinkle

Facial toner that can be used day and night

keep out or reach of the children

INDICATIONS AND USAGE

After cleansing your face, apply an appropriate amount with the clean palms until the product absorbs completely.

When using a cotton pad, pour enough amount to wet the cotton pad and clean off any left residues on your skin after cleansing from inside to outside.

WARNINGS

- For external use only.
- Do not use on damaged or broken skin.
- If any signs of the following skin troubles apprear, stop use and talk yo your dermatologist.

1. Rash
2. Itching
3. Irritation

- Avoid placing this product in this container in the excessive heat or direct sun

DOSAGE AND ADMINISTRATION

for external use only